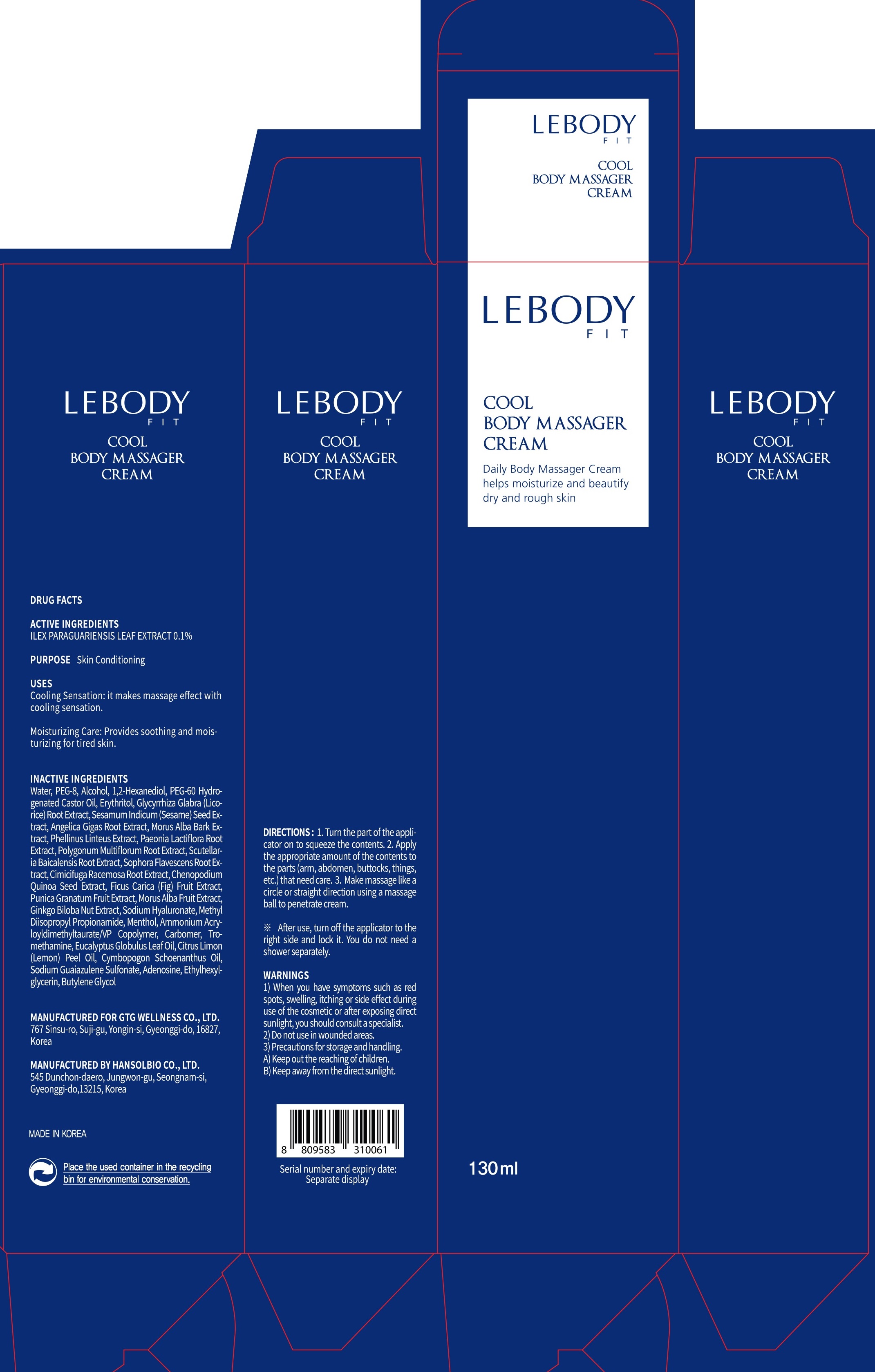 DRUG LABEL: LEBODY FIT COOL BODY MASSAGER
NDC: 71080-0005 | Form: CREAM
Manufacturer: GTG Wellness Co., Ltd.
Category: otc | Type: HUMAN OTC DRUG LABEL
Date: 20180208

ACTIVE INGREDIENTS: ILEX PARAGUARIENSIS LEAF 0.13 g/130 mL
INACTIVE INGREDIENTS: Water; Alcohol

ACTIVE INGREDIENT

Active ingredients: ILEX PARAGUARIENSIS LEAF EXTRACT 0.1%

INACTIVE INGREDIENT

Inactive ingredients: Water, PEG-8, Alcohol, 1,2-Hexanediol, PEG-60 Hydrogenated Castor Oil, Erythritol, Glycyrrhiza Glabra (Licorice) Root Extract, Sesamum Indicum (Sesame) Seed Extract, Angelica Gigas Root Extract, Morus Alba Bark Extract, Phellinus Linteus Extract, Paeonia Lactiflora Root Extract, Polygonum Multiflorum Root Extract, Scutellaria Baicalensis Root Extract, Sophora Flavescens Root Extract, Cimicifuga Racemosa Root Extract, Chenopodium Quinoa Seed Extract, Ficus Carica (Fig) Fruit Extract, Punica Granatum Fruit Extract, Morus Alba Fruit Extract, Ginkgo Biloba Nut Extract, Sodium Hyaluronate, Methyl Diisopropyl Propionamide, Menthol, Ammonium Acryloyldimethyltaurate/VP Copolymer, Carbomer, Tromethamine, Eucalyptus Globulus Leaf Oil, Citrus Limon (Lemon) Peel Oil, Cymbopogon Schoenanthus Oil, Sodium Guaiazulene Sulfonate, Adenosine, Ethylhexylglycerin, Butylene Glycol

PURPOSE

Purpose: Skin Conditioning

WARNINGS

Warnings: 1) When you have symptoms such as red spots, swelling, itching or side effect during use of the cosmetic or after exposing direct sunlight, you should consult a specialist. 2) Do not use in wounded areas. 3) Precautions for storage and handling. A) Keep out the reaching of children. B) Keep away from the direct sunlight.

KEEP OUT OF REACH OF CHILDREN

Uses

Cooling Sensation: it makes massage effect with cooling sensation.

Moisturizing Care: Provides soothing and moisturizing for tired skin.

Directions

1. Turn the part of the applicator on to squeeze the contents. 2. Apply the appropriate amount of the contents to the parts (arm, abdomen, buttocks, things, etc.) that need care. 3. Make massage like a circle or straight direction using a massage ball to penetrate cream.

* After use, turn off the applicator to the right side and lock it. You do not need a shower separately.